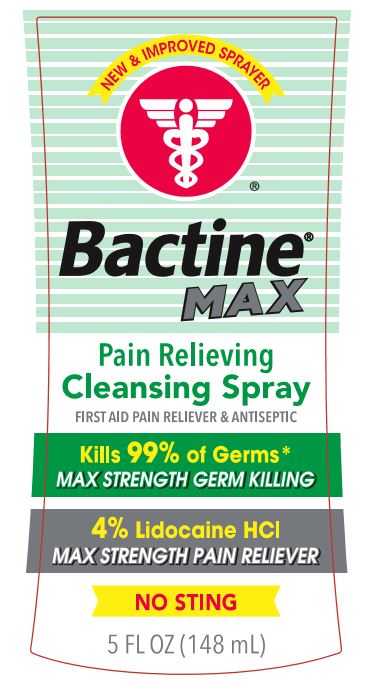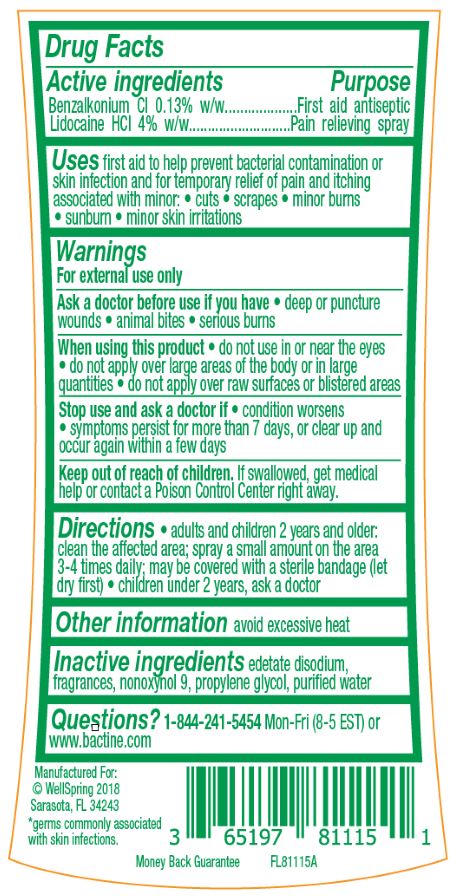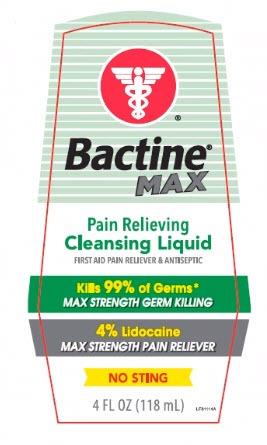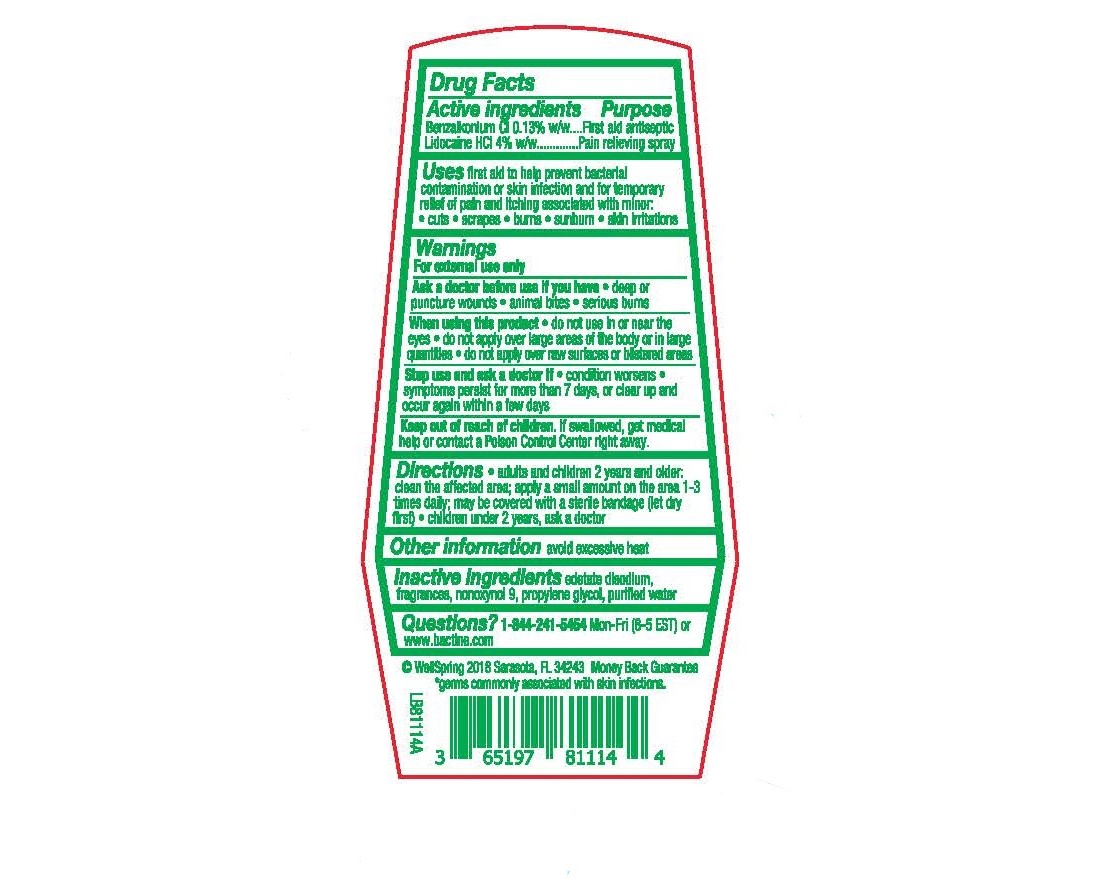 DRUG LABEL: Bactine Max
NDC: 65197-811 | Form: LIQUID
Manufacturer: WellSpring Pharmaceutical Corporation
Category: otc | Type: HUMAN OTC DRUG LABEL
Date: 20210224

ACTIVE INGREDIENTS: BENZALKONIUM CHLORIDE 0.13 g/100 mL; LIDOCAINE HYDROCHLORIDE 4 g/100 mL
INACTIVE INGREDIENTS: EDETATE DISODIUM; NONOXYNOL-9; PROPYLENE GLYCOL; WATER

Bactine® Max Pain Relieving Cleansing Spray

Drug Facts

ACTIVE INGREDIENT

Active ingredients | Purpose
Benzalkonium Cl 0.13% w/w | First aid antiseptic
Lidocaine HCl 4% w/w | Pain relieving spray

Uses

first aid to help prevent bacterial contamination or skin infection, and for temporary relief of pain and itching associated with minor:

- cuts
- scrapes
- minor burns
- sunburn
- minor skin irritations

Warnings

For external use only

Ask a doctor before use if you have

- deep or puncture wounds
- animal bites
- serious burns

When using this product

- do not use in or near the eyes
- do not apply over large areas of the body or in large quantities
- do not apply over raw surfaces or blistered areas

Stop use and ask a doctor if

- condition worsens
- symptoms persist for more than 7 days, or clear up and occur again within a few days

Keep out of reach of children. If swallowed, get medical help or contact a Poison Control Center right away.

Directions

- adults and children 2 years and older: clean the affected area; apply a small amount on the area 1-3 times daily; may be covered with a sterile bandage (let dry first)
- children under 2 years, ask a doctor

Other information

avoid excessive heat

Inactive ingredients

edetate disodium, fragrances, propylene glycol, purified water

Questions?

1-844-241-5454 Mon-Fri (8-5 EST) or www.bactine.com

Money Back Guarantee

Manufactured for: WellSpring, Sarasota, FL 34243

©2018

*germs commonly associated with skin infections.

PRINCIPAL DISPLAY PANEL - 148 mL Bottle Label

First Aid Pain Reliever & Antiseptic
Kills 99% of Germs*
Max Strength Germ Killing
4% Lidocaine HCL
Max Strength Pain Reliever
No Sting
5 FL OZ (148 mL)

PRINCIPAL DISPLAY PANEL - 118 mL Bottle Label

First Aid Pain Reliever & Antiseptic
Kills 99% of Germs*
Max Strength Germ Killing
4% Lidocaine HCL
Max Strength Pain Reliever
No Sting
4 FL OZ (118 mL)

Rear Label